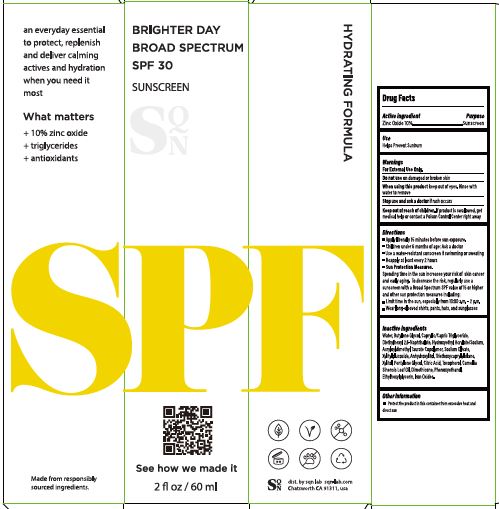 DRUG LABEL: BRIGHTER DAY BROAD SPECTRUM
NDC: 82495-101 | Form: LOTION
Manufacturer: SQN Lab
Category: otc | Type: HUMAN OTC DRUG LABEL
Date: 20220105

ACTIVE INGREDIENTS: ZINC OXIDE 10 g/100 mL
INACTIVE INGREDIENTS: DIETHYLHEXYL 2,6-NAPHTHALATE; TOCOPHEROL; ETHYLHEXYLGLYCERIN; WATER; MEDIUM-CHAIN TRIGLYCERIDES; DIMETHICONE; BUTYLENE GLYCOL; HYDROXYETHYL ACRYLATE/SODIUM ACRYLOYLDIMETHYL TAURATE COPOLYMER (45000 MPA.S AT 1%); SODIUM OLEATE; XYLITYLGLUCOSIDE; ANHYDROXYLITOL; XYLITOL; PENTYLENE GLYCOL; PHENOXYETHANOL; ANHYDROUS CITRIC ACID; FERRIC OXIDE RED; TEA LEAF OIL; TRIETHOXYCAPRYLYLSILANE

SQN - BRIGHTER DAY BROAD SPECTRUM SPF30 (82495-101)

ACTIVE INGREDIENT

ZINC OXIDE

PURPOSE

SUNSCREEN

USE

HELPS PREVENT SUNBURN

WARNINGS

FOR EXTERNAL USE ONLY.

DO NOT USE ON DAMAGED OR BROKEN SKIN.

WHEN USING THIS PRODUCT KEEP OUT OF EYES. RINSE WITH WATER TO REMOVE.

STOP USE AND ASK A DOCTOR IF RASH OCCURS.

KEEP OUT OF REACH OF CHILDREN. IF PRODUCT IS SWALLOWED, GET MEDICAL HELP OR CONTACT A POISON CONTROL CENTER RIGHT AWAY.

DIRECTIONS

- APPLY LIBERALLY 15 MINUTES BEFORE SUN EXPOSURE.
- CHILDREN UNDER 6 MONTHS OF AGE: ASK A DOCTOR.
- USE A WATER-RESISTANT SUNSCREEN IF SWIMMING OR SWEATING.
- REAPPLY AT LEAST EVERY 2 HOURS.

- SUN PROTECTION MEASURES.
  SPENDING TIME IN THE SUN INCREASES YOUR RISK OF SKIN CANCER AND EARLY AGING. TO DECREASE THE RISK, REGULARLY USE A SUNSCREEN WITH A BROAD SPECTRUM SPF VALUE OF 15 OR HIGHER AND OTHER SUN PROTECTION MEASURES INCLUDING:
- LIMIT TIME IN THE SUN, ESPECIALLY FROM 10:00 A.M. - 2 P.M.
- WEAR LONG-SLEEVED SHIRTS, PANTS, HATS, AND SUNGLASSES.

INACTIVE INGREDIENTS

WATER, BUTYLENE GLYCOL, CAPRYLIC/CAPRIC TRIGLYCERIDE, DIETHYLHEXYL 2,6-NAPHTHALATE, HYDROXYETHYL ACRYLATE/SODIUM, ACRYLOYLDIMETHYL TAURATE COPOLYMER, SODIUM OLIVATE, XYLITYLGLUCOSIDE, ANHYDROXYLITOL, TRIETHOXYCAPRYLYLSILANE, XYLITOL,PENTYLENE GLYCOL, CITRIC ACID, TOCOPHEROL, CAMELLIA SINENSIS LEAF OIL, DIMETHICONE, PHENOXYETHANOL, ETHYLHEXYLGLYCERIN, IRON OXIDES.

OTHER INFORMATION

- PROTECT THE PRODUCT IN THIS CONTAINER FROM EXCESSIVE HEAT AND DIRECT SUN.